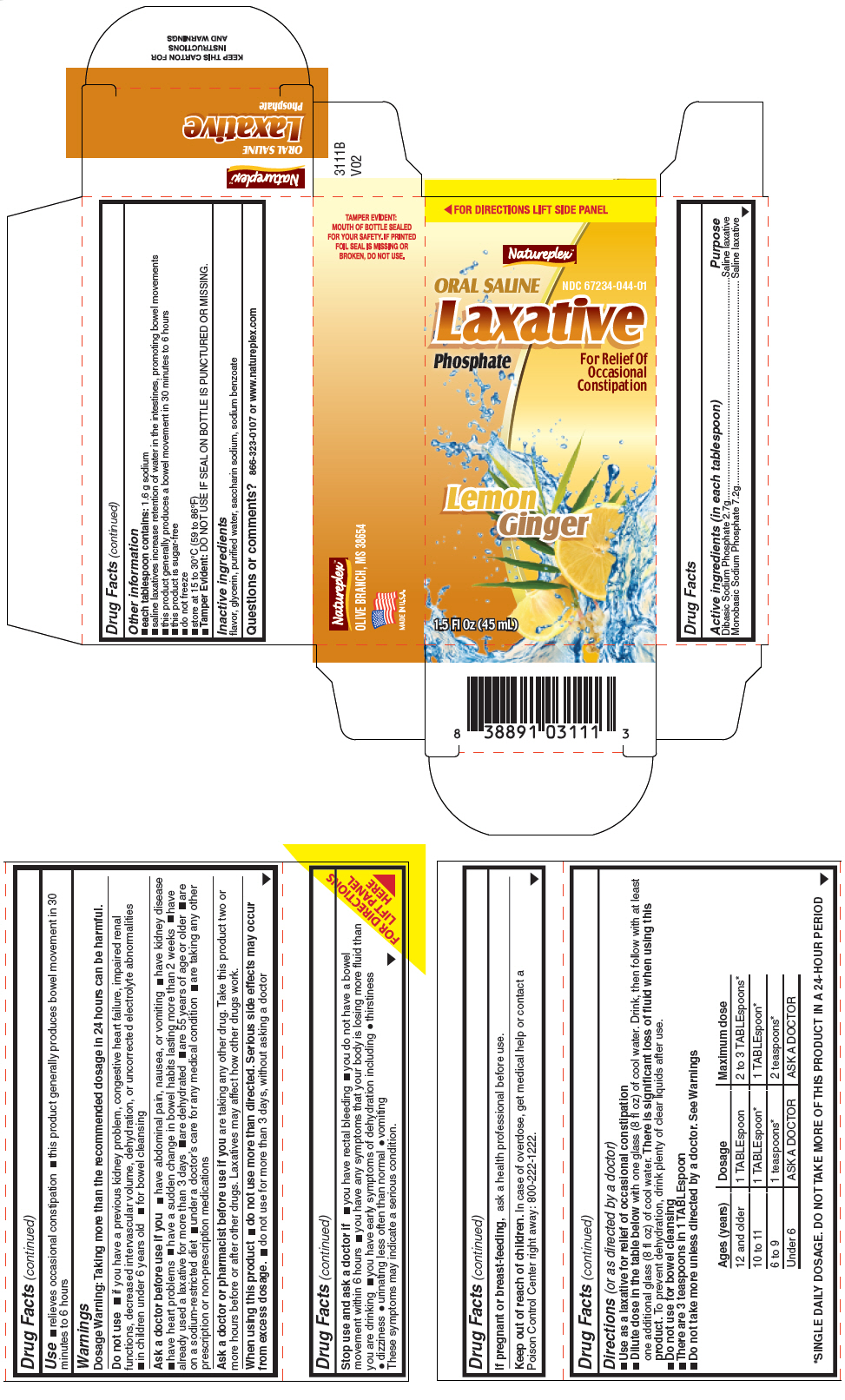 DRUG LABEL: ORAL SALINE LAXATIVE LEMON GINGER
NDC: 67234-044 | Form: LIQUID
Manufacturer: Natureplex, LLC
Category: otc | Type: HUMAN OTC DRUG LABEL
Date: 20180615

ACTIVE INGREDIENTS: SODIUM PHOSPHATE, DIBASIC, UNSPECIFIED FORM 1.4 g/14.7868 mL; SODIUM PHOSPHATE, MONOBASIC, UNSPECIFIED FORM 6.2 g/14.7868 mL
INACTIVE INGREDIENTS: GLYCERIN; WATER; SACCHARIN SODIUM; SODIUM BENZOATE

ORAL SALINE LAXATIVE LEMON GINGER

Drug Facts

ACTIVE INGREDIENT

Active ingredients (in each tablespoon) | Purpose
Dibasic Sodium Phosphate 2.7g | Saline laxative
Monobasic Sodium Phosphate 7.2g | Saline laxative

Use

- relieves occasional constipation
- this product generally produces bowel movement in 30 minutes to 6 hours

Warnings

Dosage Warning

Taking more than the recommended dosage in 24 hours can be harmful.

Do not use

- if you have a previous kidney problem, congestive heart failure, impaired renal functions, decreased intervascular volume, dehydration, or uncorrected electrolyte abnormalities
- in children under 6 years old
- for bowel cleansing

Ask a doctor before use if you

- have abdominal pain, nausea, or vomiting
- have kidney disease
- have heart problems
- have a sudden change in bowel habits lasting more than 2 weeks
- have already used a laxative for more than 3 days
- are dehydrated
- are 55 years of age or older
- are on a sodium-restricted diet
- under a doctor's care for any medical condition
- are taking any other prescription or non-prescription medications

Ask a doctor or pharmacist before use if you are taking any other drug. Take this product two or more hours before or after other drugs. Laxatives may affect how other drugs work.

When using this product

- do not use more than directed. Serious side effects may occur from excess dosage.
- do not use for more than 3 days, without asking a doctor

Stop use and ask a doctor if

- you have rectal bleeding
- you do not have a bowel movement within 6 hours
- you have any symptoms that your body is losing more fluid than you are drinking
- you have early symptoms of dehydration including
  - thirstiness
  - dizziness
  - urinating less often than normal
  - vomiting

These symptoms may indicate a serious condition.

PREGNANCY OR BREAST FEEDING

If pregnant or breast-feeding, ask a health professional before use.

Keep out of reach of children. In case of overdose, get medical help or contact a Poison Control Center right away: 800-222-1222.

Directions (or as directed by a doctor)

- Use as a laxative for relief of occasional constipation
- Dilute dose in the table below with one glass (8 fl oz) of cool water. Drink, then follow with at least one additional glass (8 fl oz) of cool water. There is significant loss of fluid when using this product. To prevent dehydration, drink plenty of clear liquids after use.
- Do not use for bowel cleansing
- There are 3 teaspoons in 1 TABLEspoon
- Do not take more unless directed by a doctor. See Warnings

Ages (years) | Dosage | Maximum dose
12 and older | 1 TABLEspoon | 2 to 3 TABLEspoons [SINGLE DAILY DOSAGE. DO NOT TAKE MORE OF THIS PRODUCT IN A 24-HOUR PERIOD]
10 to 11 | 1 TABLEspoon | 1 TABLEspoon
6 to 9 | 1 teaspoons | 2 teaspoons
Under 6 | ASK A DOCTOR | ASK A DOCTOR

Other information

- each tablespoon contains: 1.6 g sodium
- saline laxatives increase retention of water in the intestines, promoting bowel movements
- this product generally produces a bowel movement in 30 minutes to 6 hours
- this product is sugar-free
- do not freeze
- store at 15 to 30°C (59 to 86°F)
- Tamper Evident: DO NOT USE IF SEAL ON BOTTLE IS PUNCTURED OR MISSING.

Inactive ingredients

flavor, glycerin, purified water, saccharin sodium, sodium benzoate

Questions or comments?

866-323-0107 or www.natureplex.com

PRINCIPAL DISPLAY PANEL - 45 mL Bottle Carton

◀ FOR DIRECTIONS LIFT SIDE PANEL

Natureplex™

ORAL SALINE
Laxative
Phosphate
For Relief Of
Occasional
Constipation

NDC 67234-044-01

Lemon
Ginger

1.5 Fl Oz (45 mL)